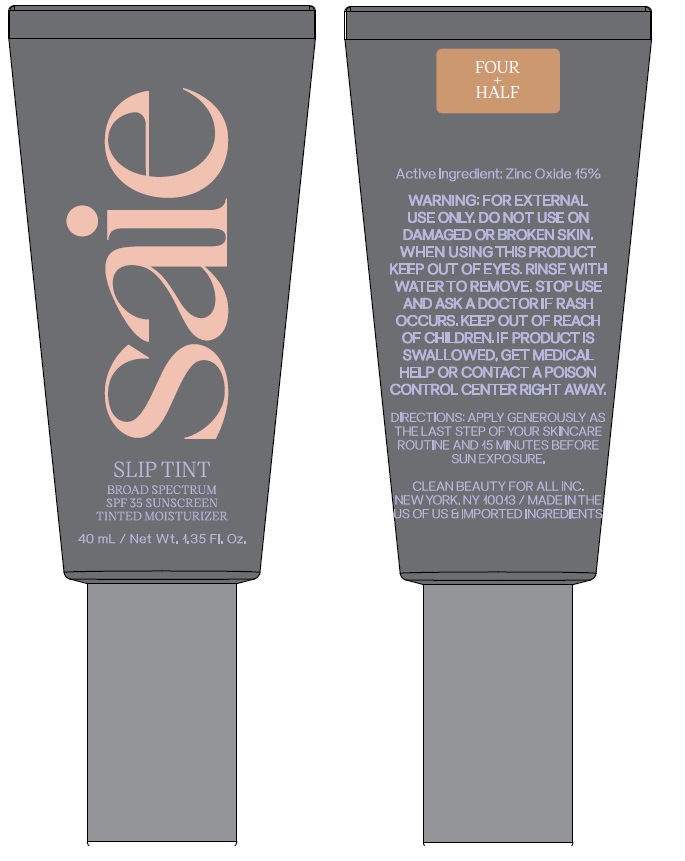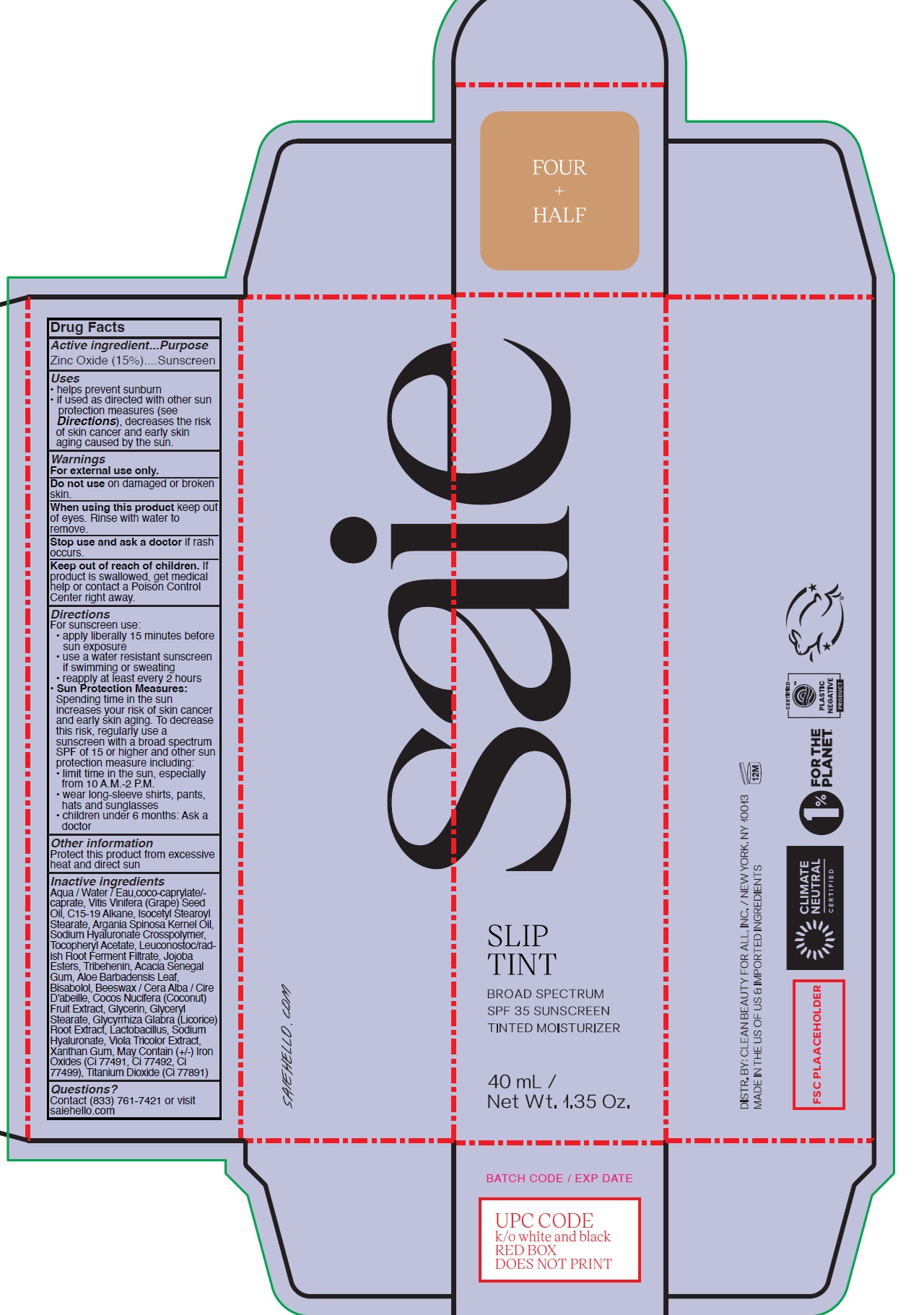 DRUG LABEL: Slip Tint Broad Spectrum SPF 35 Sunscreen Tinted Moisturizer Shade Four and Half
NDC: 90086-018 | Form: CREAM
Manufacturer: Clean Beauty For All, Inc (dba Saie)
Category: otc | Type: HUMAN OTC DRUG LABEL
Date: 20260120

ACTIVE INGREDIENTS: ZINC OXIDE 150 mg/1 mL
INACTIVE INGREDIENTS: WATER; COCOYL CAPRYLOCAPRATE; GRAPE SEED OIL; C15-19 ALKANE; ISOCETYL STEAROYL STEARATE; ARGAN OIL; .ALPHA.-TOCOPHEROL ACETATE; LEUCONOSTOC/RADISH ROOT FERMENT FILTRATE; TRIBEHENIN; ACACIA; ALOE VERA LEAF; LEVOMENOL; YELLOW WAX; COCONUT; GLYCERIN; GLYCERYL MONOSTEARATE; GLYCYRRHIZA GLABRA; BIFIDOBACTERIUM ANIMALIS LACTIS; HYALURONATE SODIUM; VIOLA TRICOLOR WHOLE; XANTHAN GUM

Slip Tint Broad Spectrum SPF 35 Sunscreen Tinted Moisturizer, Shade Four and Half

Active ingredient

Zinc Oxide (15%)

Purpose

Sunscreen

Uses

- helps prevent sunburn
- if used as directed with other sun protection measures (see Directions), decreases the risk of skin cancer and early skin aging caused by the sun.

Warnings

For external use only.

Do not use

on damaged or broken skin.

When using this product

keep out of eyes. Rinse with water to remove.

Stop use and ask a doctor

if rash occurs.

Keep out of reach of children.

If product is swallowed, get medical help or contact a Poison Control Center right away.

Directions

For sunscreen use:

- apply liberally 15 minutes before sun exposure
- use a water resistant sunscreen if swimming or sweating
- reapply at least every 2 hours
- Sun Protection Measures: Spending time in the sun increases your risk of skin cancer and early skin aging. To decrease this risk, regularly use a sunscreen with a broad spectrum SPF of 15 or higher and other sun protection measure including:
- limit time in the sun, especially from 10 A.M.-2 P.M.
- wear long-sleeve shirts, pants, hats and sunglasses
- children under 6 months: Ask a doctor

Other information

Protect this product from excessive heat and direct sun

Inactive ingredients

Aqua / Water, coco-caprylate/-caprate, Vitis Vinifera (Grape) Seed Oil, C15-19 Alkane, Isocetyl Stearoyl Stearate, Argania Spinosa Kernel Oil, Sodium Hyaluronate Crosspolymer, Tocopheryl Acetate, Leuconostoc/radish Root Ferment Filtrate, Jojoba Esters, Tribehenin, Acacia Senegal Gum, Aloe Barbadensis Leaf, Bisabolol, Beeswax / Cera Alba / Cire D'abeille, Cocos Nucifera (Coconut) Fruit Extract, Glycerin, Glyceryl Stearate, Glycyrrhiza Glabra (Licorice) Root Extract, Lactobacillus, Sodium Hyaluronate, Viola Tricolor Extract, Xanthan Gum, May Contain (+/-) Iron Oxides (Ci 77491, Ci 77492, Ci 77499), Titanium Dioxide (Ci 77891)

Questions?

Contact (833) 761-7421 or visit saiehello.com